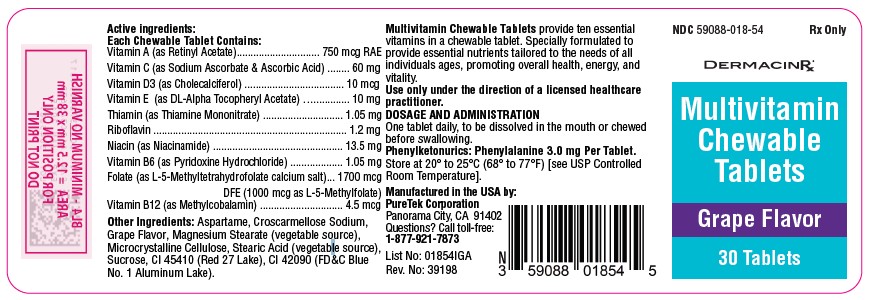 DRUG LABEL: Multivitamin
NDC: 59088-018 | Form: TABLET, CHEWABLE
Manufacturer: PureTek Corporation
Category: prescription | Type: HUMAN PRESCRIPTION DRUG LABEL
Date: 20250515

ACTIVE INGREDIENTS: VITAMIN A 750 ug/1 1; ASCORBIC ACID 24 mg/1 1; SODIUM ASCORBATE 36 mg/1 1; CHOLECALCIFEROL 10 ug/1 1; .ALPHA.-TOCOPHEROL ACETATE, DL- 10 mg/1 1; PYRIDOXINE HYDROCHLORIDE 1.05 mg/1 1; THIAMINE MONONITRATE 1.05 mg/1 1; RIBOFLAVIN 1.2 mg/1 1; NIACIN 13.5 mg/1 1; LEVOMEFOLATE CALCIUM 1000 ug/1 1; METHYLCOBALAMIN 4.5 ug/1 1
INACTIVE INGREDIENTS: SUCROSE; CROSCARMELLOSE SODIUM; D&C RED NO. 27; FD&C BLUE NO. 1; MAGNESIUM STEARATE; CELLULOSE, MICROCRYSTALLINE; STEARIC ACID; ASPARTAME

59088-018 Multivitamin Chewable Tablets

Each Chewable Tablet Contains:

Vitamin A (as Retinyl Acetate).................................... 750 mcg RAE

Vitamin C (as Sodium Ascorbate and Ascorbic Acid).............. 60 mg

Vitamin D3 (as Cholecalciferol)............................................ 10 mcg

Vitamin E (as DL-Alpha Tocopheryl Acetate)........................ 10 mg

Thiamin (as Thiamine Mononitrate).................................... 1.05 mg

Riboflavin............................................................................... 1.2 mg

Niacin (as Niacinamide)....................................................... 13.5 mg

Vitamin B6 (as Pyridoxine Hydrochloride).......................... 1.05 mg

Folate (as L-5-Methyltetrahydrofolate calcium salt)…1700 mcg DFE

(1000 mcg as L-5-Methylfolate)

Vitamin B12 (as Methylcobalamin)..................................... 4.5 mcg

Other Ingredients:

Aspartame, Croscarmellose Sodium, Grape Flavor, Magnesium Stearate (vegetable source), Microcrystalline Cellulose, Stearic Acid (vegetable source), Sucrose, CI 45410 (Red 27 Lake), CI 42090 (FD&C Blue No. 1 Aluminum Lake).

Phenylketonurics: Phenylalanine 3.0 mg Per Tablet.

INDICATIONS AND USAGE

Multivitamin Chewable Tablets is indicated to provide significant amounts of Vitamins A, C, D, E, thiamine, riboflavin, niacin, vitamin B6, vitamin B12, and folate to supplement the diet, and to help assure that nutritional deficiencies of these vitamins will not develop.

Contraindications:

This product is contraindicated in patients with known hypersensitivity to any of its ingredients.

WARNING

Keep out of the reach of children. In case of accidental overdose, seek professional assistance or contact a Poison Control Center immediately.

CAUTION: Should be chewed.

PRECAUTIONS

Folate in doses above 0.1 mg daily may obscure pernicious anemia, in that hematologic remission can occur while neurological manifestations remain progressive. There is a potential danger in administering folate to patients with undiagnosed anemia, since folate may obscure the diagnosis of pernicious anemia by alleviating the hematologic manifestations of the disease while allowing the neurologic complications to progress. This may result in severe nervous system damage before the correct diagnosis is made. Adequate doses of vitamin B12 may prevent, halt, or improve the neurologic changes caused by pernicious anemia.

The patient’s medical conditions and consumption of other drugs, herbs, and/or supplements should be considered.

Use only under the direction of a licensed healthcare practitioner. Call your doctor about side effects. To report side effects, call PureTek Corporation at 1-877-921-7873 or FDA at 1-800-FDA-1088 or www.fda.gov/medwatch.

Adverse Reactions:

Folate: Allergic sensitizations has been reported following both oral and parenteral administration of folate. Adverse reactions have been reported with specific vitamins and minerals but generally at levels substantially higher than those contained herein. However, allergic and idiosyncratic reactions are possible at lower levels.

DOSAGE AND ADMINISTRATION

One tablet daily, to be dissolved in the mouth or chewed before swallowing.

HOW SUPPLIED

Multivitamin chewable tablets are light purple with speckles, grape flavor, un-scored, round tablets. Available on prescription only in bottle of 30 tablets – NDC 59088-018-54. Dispense in a tight, light resistant container with a child resistant closure as defined in the USP/NF. All prescription substitutions using this product shall be pursuant to state statutes as applicable. This is not an Orange Book product.

STORAGE

Do not use if bottle seal is broken. KEEP THIS AND ALL MEDICATIONS OUT OF THE REACH OF CHILDREN.

Store at 20° to 25°C (68° to 77°F) [see USP Controlled Room Temperature].

Multivitamin Chewable Tablets

Manufactured in the USA by:

PureTek Corporation

Panorama City, CA 91402

Questions? Call toll-free:

1-877-921-7873